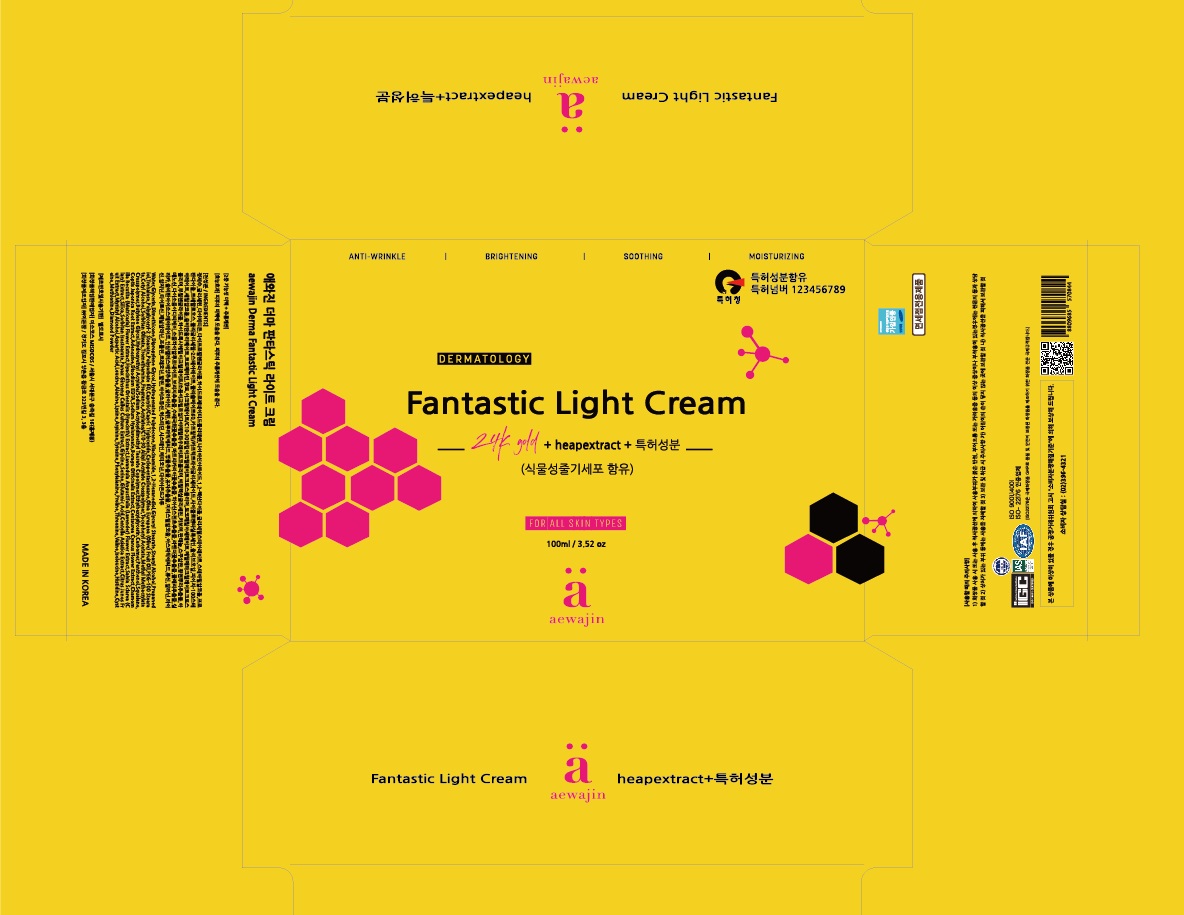 DRUG LABEL: Fantastic LightCream
NDC: 73466-0008 | Form: CREAM
Manufacturer: MISOCOS
Category: otc | Type: HUMAN OTC DRUG LABEL
Date: 20230406

ACTIVE INGREDIENTS: NIACINAMIDE 0.3 g/100 mL
INACTIVE INGREDIENTS: WATER; GLYCERIN

ACTIVE INGREDIENT

Hydrogenated Polydecene,Niacinamide

PURPOSE

skin protectant

KEEP OUT OF REACH OF THE CHILDREN

WARNINGS

■ For external use only.

■ Do not use in eyes.

■ lf swallowed, get medical help promptly.

■ Stop use, ask doctor lf irritation occurs.

■ Keep out of reach of children.

DOSAGE AND ADMINISTRATION

for external use only

INACTIVE INGREDIENT

Water,Glycerin,Dimethicone,Dipropylene Glycol,1,2-Hexanediol,Glyceryl Stearate,Stearyl Alcohol,Propanediol,Trehalose,Polyglyceryl-2 Stearate,Polysorbate 60,Caprylic/CapricTriglyceride,Cyclopentasiloxane,Olea Europaea (Olive) Fruit Oil,PEG-100 Stearate,Cetyl Alcohol,Sorbitan Olivate,Tromethamine,Fragrance,Acrylates/C10-30 Alkyl Acrylate Crosspolymer,Tocopheryl Acetate,Methyl Methacrylate Crosspolymer,Butylene Glycol,Hydroxyethyl Acrylate/Sodium Acryloyldimethyl Taurate Copolymer,Ethylhexylglycerin,Carbomer,Panthenol,Squalane,

Coptis Japonica Root Extract,Adenosine,Disodium EDTA,Sodium Hyaluronate,Borago Officinalis Extract,Centaurea Cyanus Flower Extract,Chamomilla Recutita (Matricaria) Flower Extract,Hyacinthus Orientalis (Hyacinth) Extract,Lavandula Angustifolia (Lavender) Flower Extract,Salvia Sclarea (Clary) Extract,Silica,Sorbitan Isostearate,Panax Ginseng Callus Culture Extract,Glycine,Serine,Glutamic Acid,Centella Asiatica Extract,Citrus Junos Fruit Extract,Myristyl Alcohol,Aspartic Acid,Leucine,Alanine,Lysine,Arginine,Tyrosine,Phenylalanine,Proline,Threonine,Valine,Isoleucine,Histidine,Cysteine,Methionine,Diamond Powder

INDICATIONS AND USAGE

take proper amount to the skin when needed